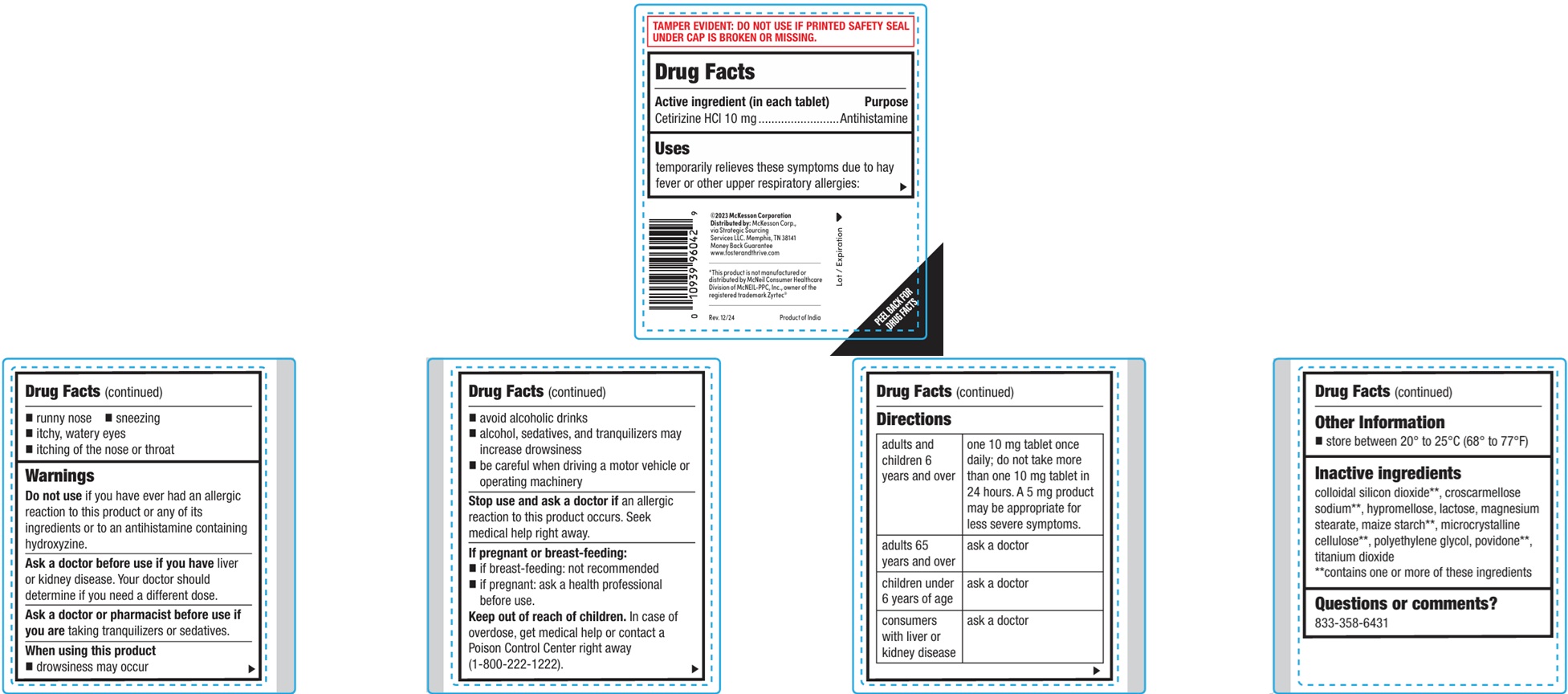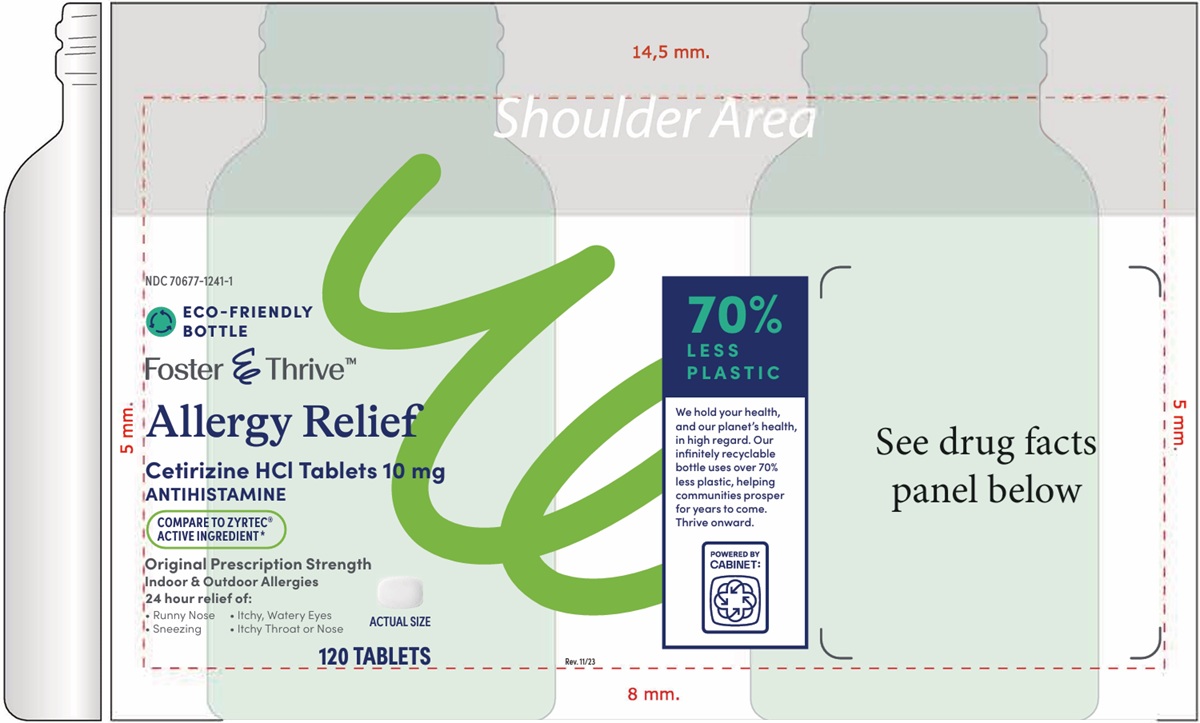 DRUG LABEL: Allergy Relief
NDC: 70677-1241 | Form: TABLET, FILM COATED
Manufacturer: Strategic Sourcing Services LLC
Category: otc | Type: HUMAN OTC DRUG LABEL
Date: 20260129

ACTIVE INGREDIENTS: CETIRIZINE HYDROCHLORIDE 10 mg/1 1
INACTIVE INGREDIENTS: SILICON DIOXIDE; CROSCARMELLOSE SODIUM; HYPROMELLOSE, UNSPECIFIED; LACTOSE, UNSPECIFIED FORM; MAGNESIUM STEARATE; MAIZE INVERT SUGAR; MICROCRYSTALLINE CELLULOSE; POLYETHYLENE GLYCOL, UNSPECIFIED; POVIDONE; TITANIUM DIOXIDE

Allergy Relief (Cetirizine HCl Tablets)

Warnings

Do not useif you have ever had an allergic reaction to this product or any of its ingredients or to an antihistamine containing hydroxyzine.